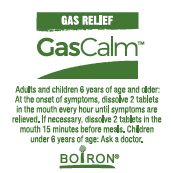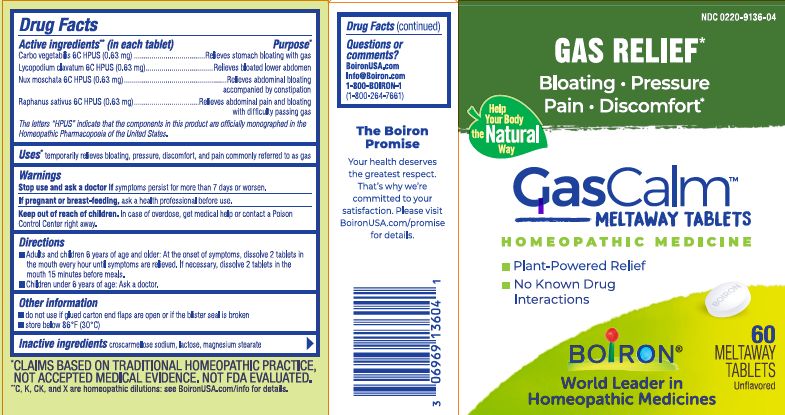 DRUG LABEL: GasCalm
NDC: 0220-9136 | Form: TABLET
Manufacturer: Boiron
Category: homeopathic | Type: HUMAN OTC DRUG LABEL
Date: 20241114

ACTIVE INGREDIENTS: NUTMEG 6 [hp_C]/1 1; LYCOPODIUM CLAVATUM SPORE 6 [hp_C]/1 1; ACTIVATED CHARCOAL 6 [hp_C]/1 1; RADISH 6 [hp_C]/1 1
INACTIVE INGREDIENTS: CROSCARMELLOSE SODIUM; LACTOSE; MAGNESIUM STEARATE

GasCalm tablets

Active ingredients** (in each tablet)

Carbo vegetabilis 6C HPUS (0.63 mg)

Lycopodium clavatum 6C HPUS (0.63 mg)

Nux moschata 6C HPUS (0.63 mg)

Raphanus sativus 6C HPUS (0.63 mg)

The letters “HPUS” indicate that the components in this product are officially monographed in the Homeopathic Pharmacopoeia of the United States.

Purpose*

Carbo vegetabilis 6C HPUS ...Relieves stomach bloating with gas
Lycopodium clavatum 6C HPUS ... Relieves bloated lower abdomen
Nux moschata 6C HPUS... Relieves abdominal bloating accompanied by constipation
Raphanus sativus 6C HPUS... Relieves abdominal pain and bloating with difficulty passing gas

Uses*

temporarily relieves bloating, pressure, discomfort, and pain commonly referred to as gas

Stop use and ask a doctor if symptoms persist continuously for more than 7 days or worsen.

PREGNANCY OR BREAST FEEDING

If pregnant or breast-feeding, ask a health professional before use.

Keep out of reach of children. In case of overdose, get medical help or contact a Poison Control Center right away.

DOSAGE AND ADMINISTRATION

- Adults and children 6 years of age and older: At the onset of symptoms, dissolve 2 tablets in the mouth every hour until symptoms are relieved. If necessary, dissolve 2 tablets in the mouth 15 minutes before meals.
- Children under 6 years of age: Ask a doctor.

INACTIVE INGREDIENT

croscarmellose sodium, lactose, magnesium stearate

QUESTIONS

BoironUSA.com
Info@Boiron.com
1-800-BOIRON-1
(1-800-264-7661)

Made in France

Distributed by Boiron, Inc.

Newtown Square, PA 19073

do not use if glued carton and flaps are open or if the blister seal is broken

store below 86°F (30° C)

Plant-Powered Relief

No Known Drug Interactions

60 Meltaway Tablets, unflavored

*CLAIMS BASED ON TRADITIONAL HOMEOPATHIC PRACTICE, NOT ACCEPTED MEDICAL EVIDENCE. NOT FDA EVALUATED.

**C, K, CK, and X are homeopathic dilutions: see BoironUSA.com/info for details.